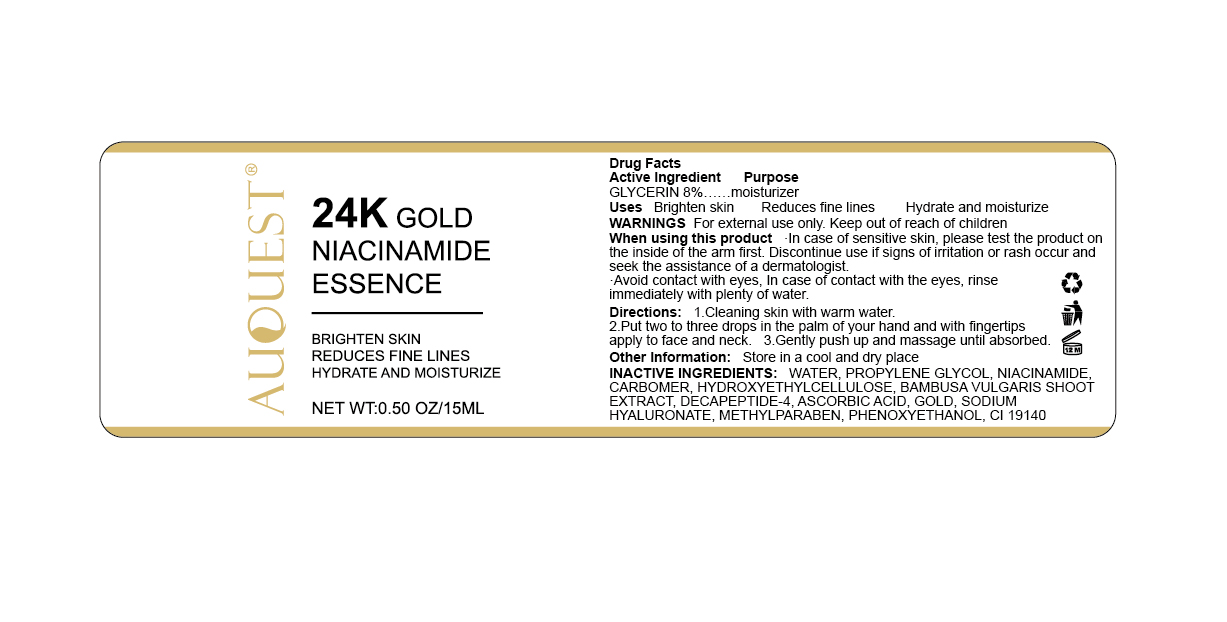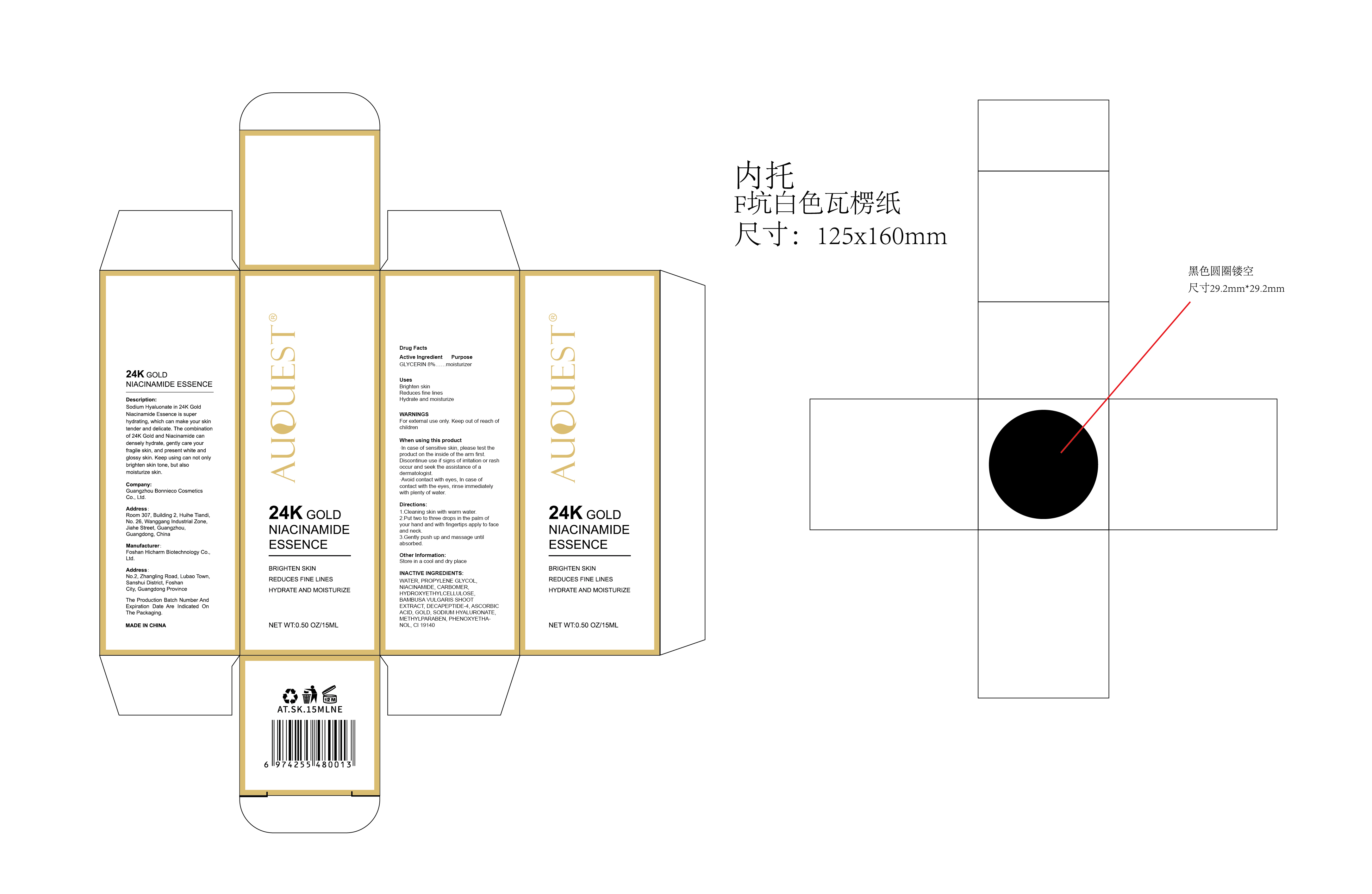 DRUG LABEL: AuQuest 24K GOLD NIACINAMIDE ESSENCE
NDC: 84186-001 | Form: LIQUID
Manufacturer: Guangzhou Bonnieco Cosmetics Co., Ltd
Category: otc | Type: HUMAN OTC DRUG LABEL
Date: 20240319

ACTIVE INGREDIENTS: GLYCERIN 8 g/100 mL
INACTIVE INGREDIENTS: GOLD; METHYLPARABEN; PHENOXYETHANOL; ASCORBIC ACID; HYALURONATE SODIUM; WATER; HYDROXYETHYL CELLULOSE, UNSPECIFIED; BAMBUSA VULGARIS STEM; FD&C YELLOW NO. 5; CARBOMER HOMOPOLYMER, UNSPECIFIED TYPE; ACETYL DECAPEPTIDE-3; PROPYLENE GLYCOL; NIACINAMIDE

84186-001

Active Ingredient

GLYCERIN 8%

Purpose

Brighten skin
Reduces fine lines
Hydrate and moisturize

Use

Apply gently to skin and spread evenly

Warnings

For external use only. Keep out of reach of children

When Using

·In case of sensitive skin, please test the product on the inside of the arm first. Discontinue use if signs of irritation or rash occur and seek the assistance of a dermatologist.
·Avoid contact with eyes, In case of contact with the eyes, rinse immediately with plenty of water.

Keep Oot Of Reach Of Children

If swallowed, get medical help or contact a poison control center right away.

Directions

1.Cleaning skin with warm water.
2.Put two to three drops in the palm of your hand and with fingertips apply to face and neck.
3.Gently push up and massage until absorbed.

Other information

Description:
Sodium Hyaluonate in 24K GoldNiacinamide Essence is super hydrating, which can make your skin tender and delicate. The combination of 24K Gold and Niacinamide can densely hydrate, gently care your fragile skin, and present white and glossy skin. Keep using can not only brighten skin tone, but also moisturize skin.

Inactive ingredients

WATER, PROPYLENE GLYCOL, NIACINAMIDE, CARBOMER, HYDROXYETHYLCELLULOSE, BAMBUSA VULGARIS SHOOT EXTRACT, DECAPEPTIDE-4, ASCORBIC ACID, GOLD, SODIUM HYALURONATE, METHYLPARABEN, PHENOXYETHANOL, CI 19140

PACKAGE LABEL

PRINCIPAL DISPLAY PANEL